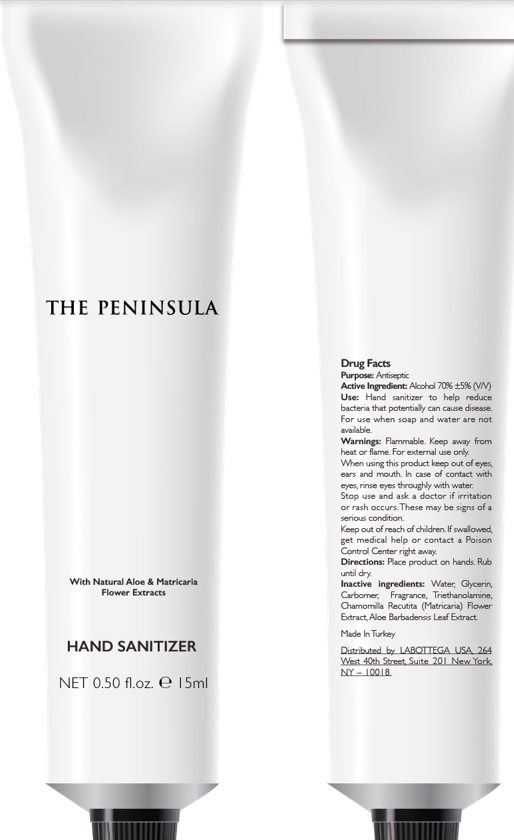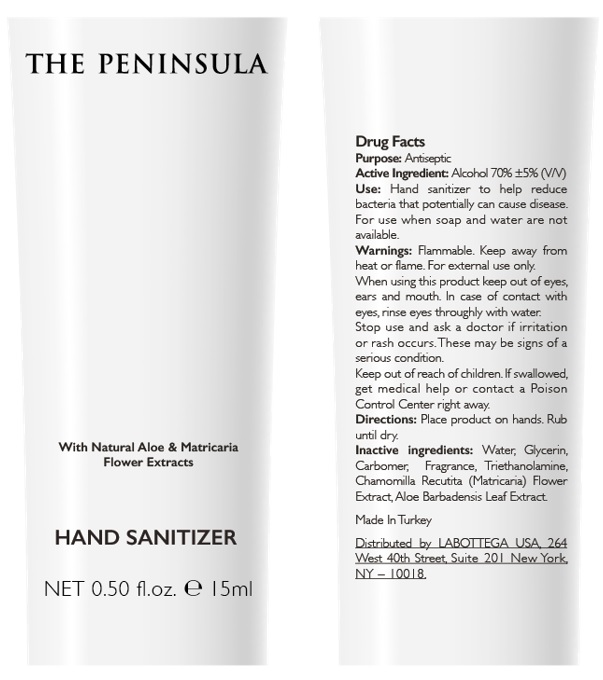 DRUG LABEL: THE PENINSULA HAND SANITIZER
NDC: 80176-004 | Form: GEL
Manufacturer: CERCI KOZMETIK VE OTEL EKIPMANLARI PAZARLAMA IC VE DIS TICARET LIMITED SIRKETI
Category: otc | Type: HUMAN OTC DRUG LABEL
Date: 20231026

ACTIVE INGREDIENTS: ALCOHOL 70 mL/100 mL
INACTIVE INGREDIENTS: WATER; GLYCERIN; CARBOMER HOMOPOLYMER TYPE C; TROLAMINE; CHAMOMILE FLOWER OIL; ALOE VERA LEAF; METHYL BENZOATE

Drug Facts

Active Ingredient

Alcohol 70% v/v +/-5%V/V

Purpose

Antiseptic

Use

Hand Sanitizer to help reduce bacteria that potentially can cause disease. For use when soap and water are not available.

Warnings

For external use only. Flammable. Keep away from heat or flame

WHEN USING

When using this products keepout of eyes, ears, and mouth. In case of contact with eyes, rinse eyes thoroughly with water.

Stop use and ask a doctor ifirritation or rash occurs. These may be signs of a serious condition.

Keep out of reach of children. If swallowed, get medical help or contact a Poison Control Center right away.

Directions

- Place enough product on hands.Rub hands until dry.

Inactive ingredients

Carbomer, Glycerin, Purified Water, Triethanolamine, Fragrance, Chamomilla recutita [Matricaria] Flower Extract, Aloe Barbadensis Leaf Extract